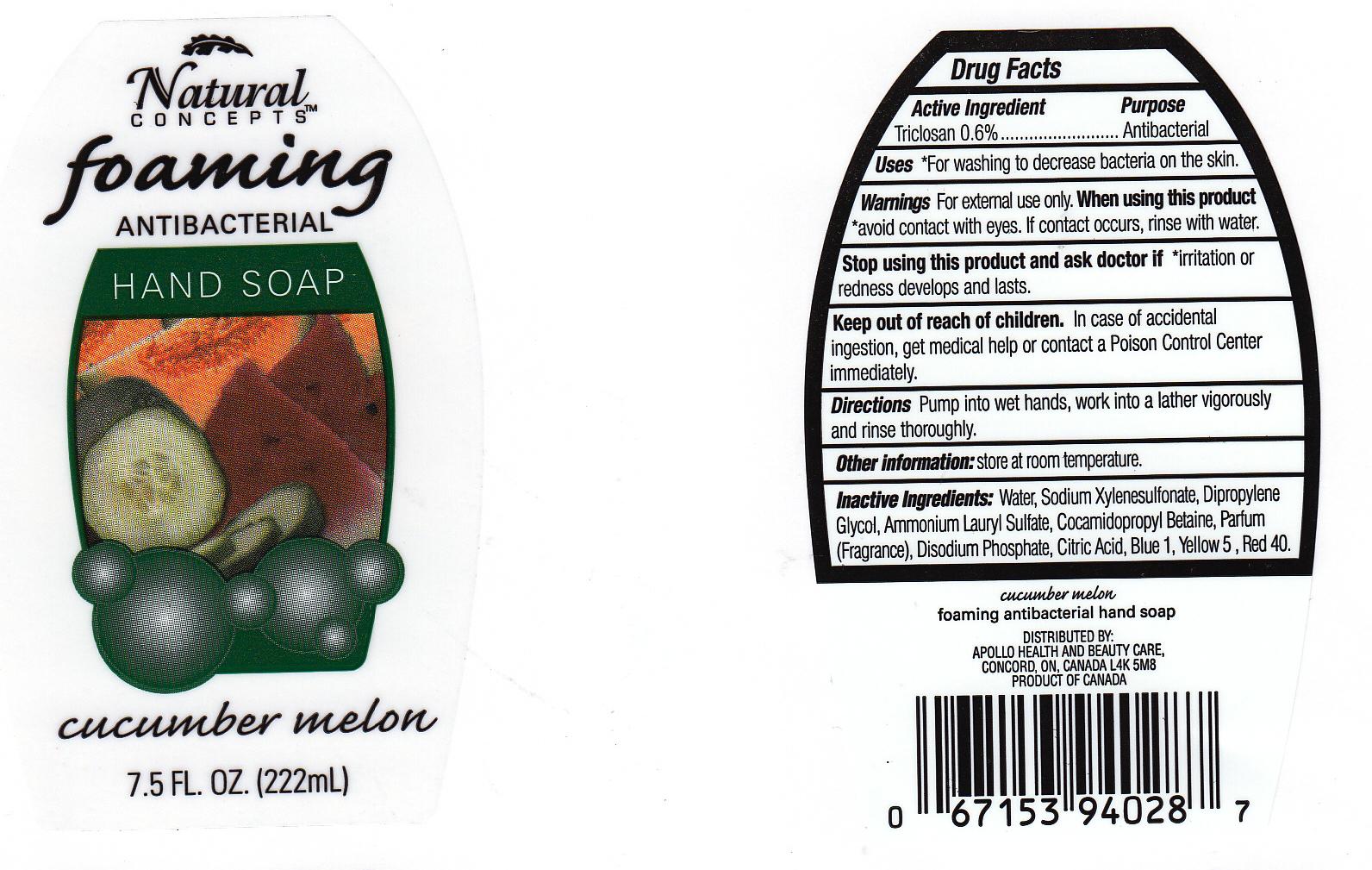 DRUG LABEL: Foaming Antibacterial 
NDC: 63148-167 | Form: LIQUID
Manufacturer: Apollo Health and Beauty Care
Category: otc | Type: HUMAN OTC DRUG LABEL
Date: 20111026

ACTIVE INGREDIENTS: TRICLOSAN 0.6 mL/100 mL
INACTIVE INGREDIENTS: WATER; SODIUM XYLENESULFONATE; DIPROPYLENE GLYCOL; AMMONIUM LAURYL SULFATE; COCAMIDOPROPYL BETAINE; SODIUM PHOSPHATE, DIBASIC; CITRIC ACID MONOHYDRATE; FD&C BLUE NO. 1; FD&C YELLOW NO. 5; FD&C RED NO. 40

Drug Facts Box - Back Label

Active Ingredient

Triclosan 0.6%

Purpose

Antibacterial

Uses

*For washing to decrease bacteria on the skin.

WARNINGS

For external use only.

When using this product

*avoid contact with eyes. If contact occurs, rinse with water.

Stop using this product and ask doctor if

if irritation or redness develops and lasts.

Keep out of reach of children

In case of accidental ingestion, get medical help or contact Poison Control Center immediately.

Directions

Pump into wet hands, work into a lather vigorously and rinse thoroughly.

Other information

Store at room temperature.

Inactive ingredients

Water, Sodium Xylenesulfonate, Dipropylene Glycol, Ammonium Lauryl Sulfate, Cocamidopropyl Betaine, Fragrance, Disodium Phosphate, Citric Acid, Blue 1 (CI 42090), Yellow 5 (CI 19140), Red 40 (CI 16035).